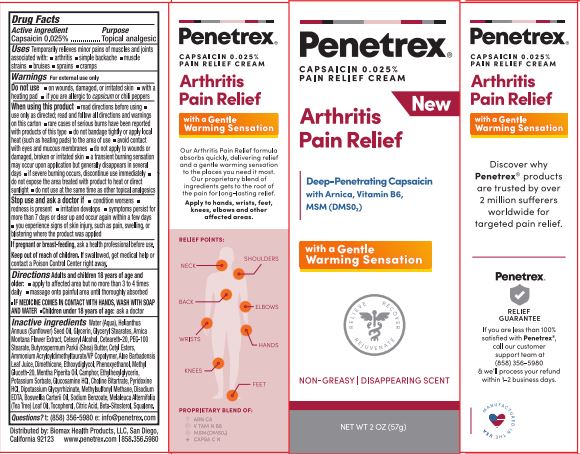 DRUG LABEL: Penetrex(r) Arthritis Pain Relief
NDC: 62742-4216 | Form: CREAM
Manufacturer: Allure Labs
Category: otc | Type: HUMAN OTC DRUG LABEL
Date: 20220620

ACTIVE INGREDIENTS: CAPSAICIN 0.025 g/100 g
INACTIVE INGREDIENTS: TEA TREE OIL; AMMONIUM ACRYLOYLDIMETHYLTAURATE; ALOE VERA LEAF; CAMPHOR (NATURAL); FRANKINCENSE OIL; TOCOPHEROL; SUNFLOWER OIL; CETOSTEARYL ALCOHOL; PEG-100 STEARATE; SHEA BUTTER; PEPPERMINT OIL; GLUCOSAMINE HYDROCHLORIDE; PYRIDOXINE HYDROCHLORIDE; POTASSIUM SORBATE; WATER; GLYCERIN; ETHYLHEXYLGLYCERIN; GLYCYRRHIZINATE DIPOTASSIUM; EDETATE DISODIUM ANHYDROUS; GLYCERYL MONOSTEARATE; PHENOXYETHANOL; POLYOXYL 20 CETOSTEARYL ETHER; DIMETHICONE; CITRIC ACID MONOHYDRATE; SODIUM BENZOATE; DIETHYLENE GLYCOL MONOETHYL ETHER; CHOLINE BITARTRATE; .BETA.-SITOSTEROL; SQUALENE; CETYL ESTERS WAX; METHYL GLUCETH-20; ARNICA MONTANA FLOWER; DIMETHYL SULFONE

Drug Facts

Active ingredient

Capsaicin 0.025%

Purpose

Topical analgesic

Uses

Temporarily relieves minor pains of muscles and joints associated with arthritis,simple backache,muscle strains,bruises,sprains,cramps

Warnings

For external use only

Do not use

on wounds, damaged, or irritated skin

with a heating pad

if you are alergic to capsicum or chili peppers

When using this product

Read directions befbre using

use only as directed; read and follow all directions and warnings on this carton rare cases of serious bums have been reported with products of this type

do not bandage tightly or apply local heat (such as heating pads) to the area of use

avoid contact with eyes and mucous membranes

do not apply to wounds or damaged, broken or irritated skin

a transient burning sensation may occur upon application but generally disappears in several days

if severe burning occurs, discontinue use immediately

do not expose the area treated With product to heat or direct sunlight

do not use at the same time as other topical analgesics,

Stop use and ask a doctor if

condition worsens

redness is present

irritation develops

symptoms persist for more than 7 days or clear up and occur again within a few days

you experience signs of skin injury, such as pain, swelling, or blistering where the product was applied

Keep out of reach of children.

If swalowed, get medical help or contact a Poison Control Center right away.

Directions:

Adults and children 18 years of age and older:

apply to affected area but no more than 3 to 4 times daily

massage onto painful area until thoroughly absorbed

IF MEDICINE COMES IN CONTACT WITH HANDS, WASH WITH SOAP AND WATER

Children under 18 years of age: ask a doctor

OTHER SAFETY INFORMATION

If pregnant or breast-feeding, ask a health professional before use

Inactive ingredients:

Water (Aqua),Helanthus Annuus (Sunflower) Seed Oil, Glycerin,GlycerylStearates, Amica Montana Flower Extract,

Cetearyl Alcohol,Ceteareth-20,PEG-100 Stearate, Butyrospermum Parkii (Shea) Buffer,Cetyl Esters,Ammonium Acryloyldimethyltaurate/VP Copolymer, Aloe Barbadensis Leaf Juice,Dimethicone, Ethoxydiglycol, Phenoxyethanol,

Methyl Gluceth-20,Menthe Piperita Oil,Camphor,Ethylhexylglycerin,Potassium Sorbate, Glucosamine HCI,Choline Bitartrate,

Pyridoxine HCL, Glycyrrhizinate Dipotassium, Methyl sulfonyl Methane,Disodium EDTA, Boswellia carterii oil,

Sodium Benzoate, Melaleuca Alternifolia (Tea Tree) Leaf Oil, Tocopherol, Citric Acid,Beta-Sitosterol, Squalene.